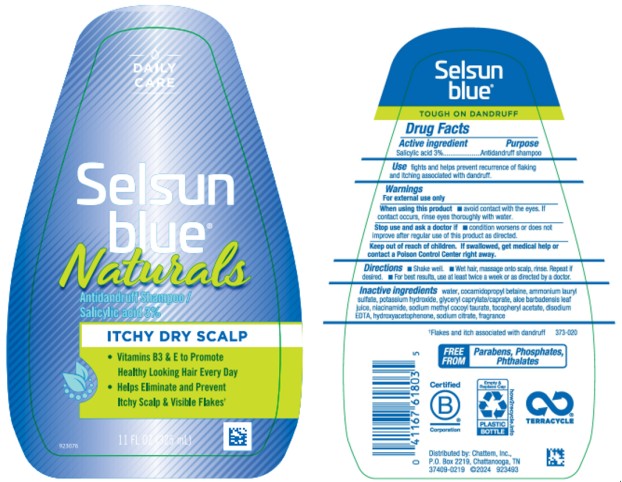 DRUG LABEL: Selsun Blue Naturals Itchy, Dry Scalp
NDC: 41167-6180 | Form: SHAMPOO
Manufacturer: Chattem, Inc.
Category: otc | Type: HUMAN OTC DRUG LABEL
Date: 20260218

ACTIVE INGREDIENTS: SALICYLIC ACID 0.03 g/1 mL
INACTIVE INGREDIENTS: WATER; COCAMIDOPROPYL BETAINE; AMMONIUM LAURYL SULFATE; POTASSIUM HYDROXIDE; GLYCERYL CAPRYLATE/CAPRATE; ALOE VERA LEAF; NIACINAMIDE; SODIUM METHYL COCOYL TAURATE; ALPHA-TOCOPHEROL ACETATE; EDETATE DISODIUM; HYDROXYACETOPHENONE; SODIUM CITRATE

Selsun Blue Naturals Shampoo - Itchy, Dry Scalp

Drug Facts
Selsun blue Naturals Itchy Dry Scalp

Active ingredient

Salicylic Acid 3%

Purpose

Anti-dandruff

Use

fights and help prevent recurrence of flaking and itching associated with dandruff

Warnings

For external use only

When using this product

- avoid contact with eyes. If contact occurs, rinse eyes thoroughly with water.

Stop use and ask a doctor if

- condition worsens or does not improve after regular use of this product as directed

Keep out of reach of children.

If swallowed, get medical help or contact a Poison Control Center right away.

Directions

- Shake well.
- Wet hair, massage onto scalp, rinse. Repeat if desired.
- For best results, use at least twice a week or as directed by a doctor

Inactive ingredients

water, cocamidopropyl betaine, ammonium lauryl sulfate, potassium hydroxide, glyceryl caprylate/caprate, aloe barbadensis leaf juice, niacinamide, sodium methyl cocoyl taurate, tocopheryl acetate, disodium EDTA, hydroxyacetophenone, sodium citrate, fragrance

PRINCIPAL DISPLAY PANEL

DAILY CARE
Selsun blue®
Naturals
Antidandruff Shampoo Salicylic acid 3%
ITCHY DRY SCALP
11 FL OZ (325 mL)